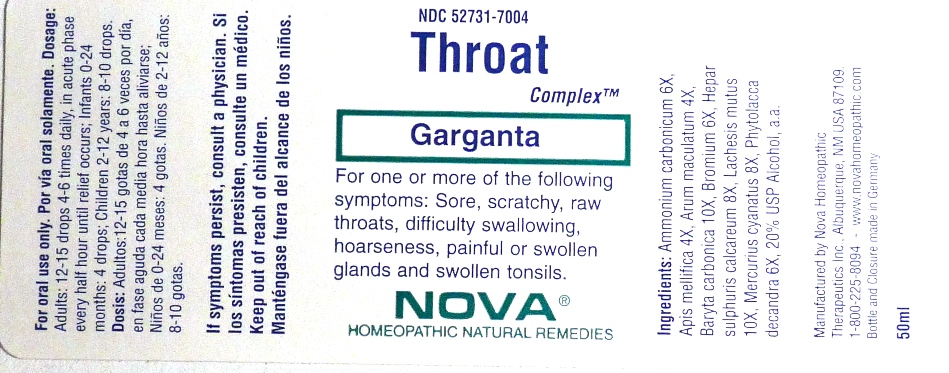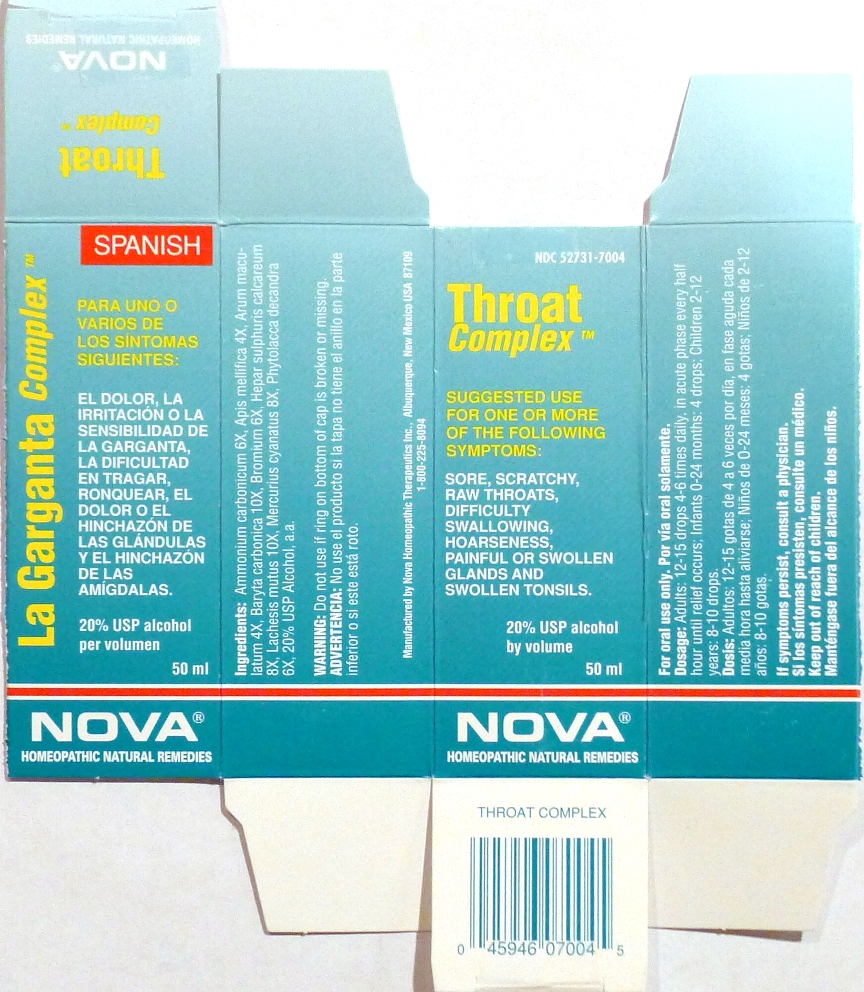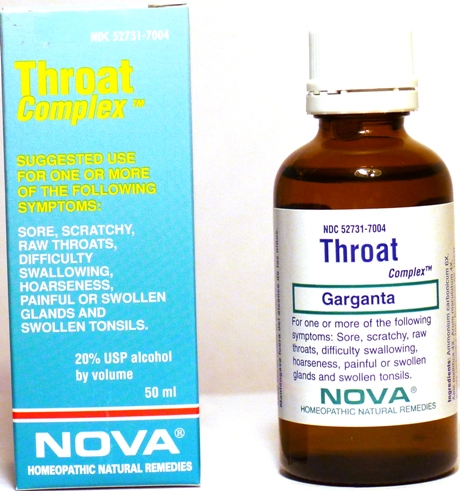 DRUG LABEL: Throat Complex
NDC: 52731-7004 | Form: LIQUID
Manufacturer: Nova Homeopathic Therapeutics, Inc.
Category: homeopathic | Type: HUMAN OTC DRUG LABEL
Date: 20110601

ACTIVE INGREDIENTS: AMMONIUM CARBONATE 6 [hp_X]/1 mL; APIS MELLIFERA 4 [hp_X]/1 mL; ARUM MACULATUM ROOT 4 [hp_X]/1 mL; BARIUM CARBONATE 10 [hp_X]/1 mL; BROMINE 6 [hp_X]/1 mL; CALCIUM SULFIDE 8 [hp_X]/1 mL; LACHESIS MUTA VENOM 10 [hp_X]/1 mL; MERCURIC CYANIDE 8 [hp_X]/1 mL; PHYTOLACCA AMERICANA ROOT 6 [hp_X]/1 mL
INACTIVE INGREDIENTS: ALCOHOL

Throat Complex

Purpose:

Suggested use for one or more of the following symptoms:
Sore, scratchy, raw throats, difficulty swallowing, hoarseness, painful or swollen glands and swollen tonsils.

Usage and Dosage:

For oral use only.

DOSAGE AND ADMINISTRATION

Adults:
In Acute Phase:
12-15 drops, every half hour until relief occurs
When Relief Occurs:
12-15 drops, 4-6 times per day
Children 2-12 years:
8-10 drops, 4-6 times per day
Infants 0-24 months:
4 drops, 4-6 times per day

Warnings:

Keep out of reach of children.

WARNINGS

If symptoms persist, consult a physician.
Do not use if ring on bottom of cap is broken or missing.

Active Ingredients:

Ammonium carbonicum 6X, Apis mellifica 4X, Arum maculatum 4X, Baryta carbonica 10X, Bromium 6X, Hepar sulphuris calcareum 8X, Lachesis mutus 10X, Mercurius cyanatus 8X, Phytolacca decandra 6X

Inactive Ingredients:

Alcohol, 20% USP

QUESTIONS

Manufactured by Nova Homeopathic Therapeutics Inc., Albuquerque, New Mexico USA 87109
1-800-225-8094

PACKAGE LABEL

Throat Complex Product
Throat Complex Bottle Label
Throat Complex Box